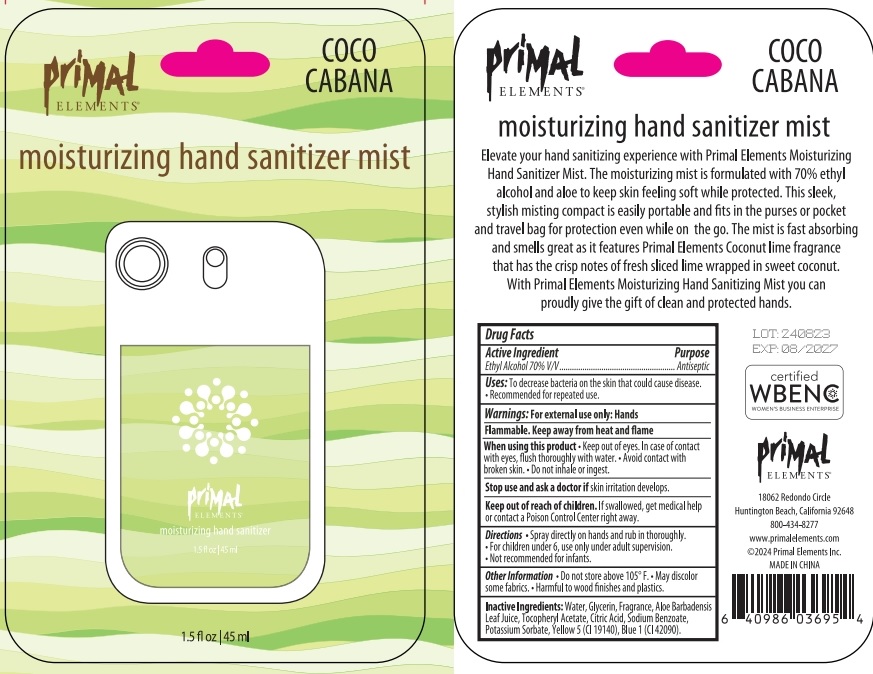 DRUG LABEL: Primal Elements Moisturizing Hand Sanitizer mist - Coco Cabana
NDC: 75262-012 | Form: SPRAY
Manufacturer: ZheJiang Eshine Cosmetic Co Ltd
Category: otc | Type: HUMAN OTC DRUG LABEL
Date: 20240821

ACTIVE INGREDIENTS: ALCOHOL 70 mL/100 mL
INACTIVE INGREDIENTS: WATER; SODIUM BENZOATE; .ALPHA.-TOCOPHEROL ACETATE, D-; GLYCERIN; POTASSIUM SORBATE; FD&C YELLOW NO. 5; FD&C BLUE NO. 1

Primal Elements Moisturizing Hand Sanitizer mist - Coco Cabana

Purpose

Antiseptic

Use

- To decrease bacteria on the skin that could cause disease.
- Recommended for repeaed use.

Warnings

For external use only: hands

Flammable.Keep away from heat and flame.

When using this product

- Keep out of eyes. In case of contact with eyes, flush thoroughly with water.
- Avoid contact with broken skin.
- Do not inhale or ingest.

Stop use and ask a doctor if

skin irritation develops.

Other Information

- Do not store above 105℉.
- May discolor some fabrics.
- Harmful to wood finisheds and plastics.

Keep out of reach of children.

If swallowed, get medical help or contact a Poison Control Center right away.

Directions

- Spray directly on hands and rub in thoroughly.
- For children under 6, use only under adult supervision.
- Not recommended for infants.

Inactive ingredients

Water, Glycerin, Aloe Barbadensis Leaf Extract, Tocopheryl Acetate, Citric Acid, Sodium Benzoate, Potassium Sorbate, Red 40 (CI 16035)

Call 800-434-8277